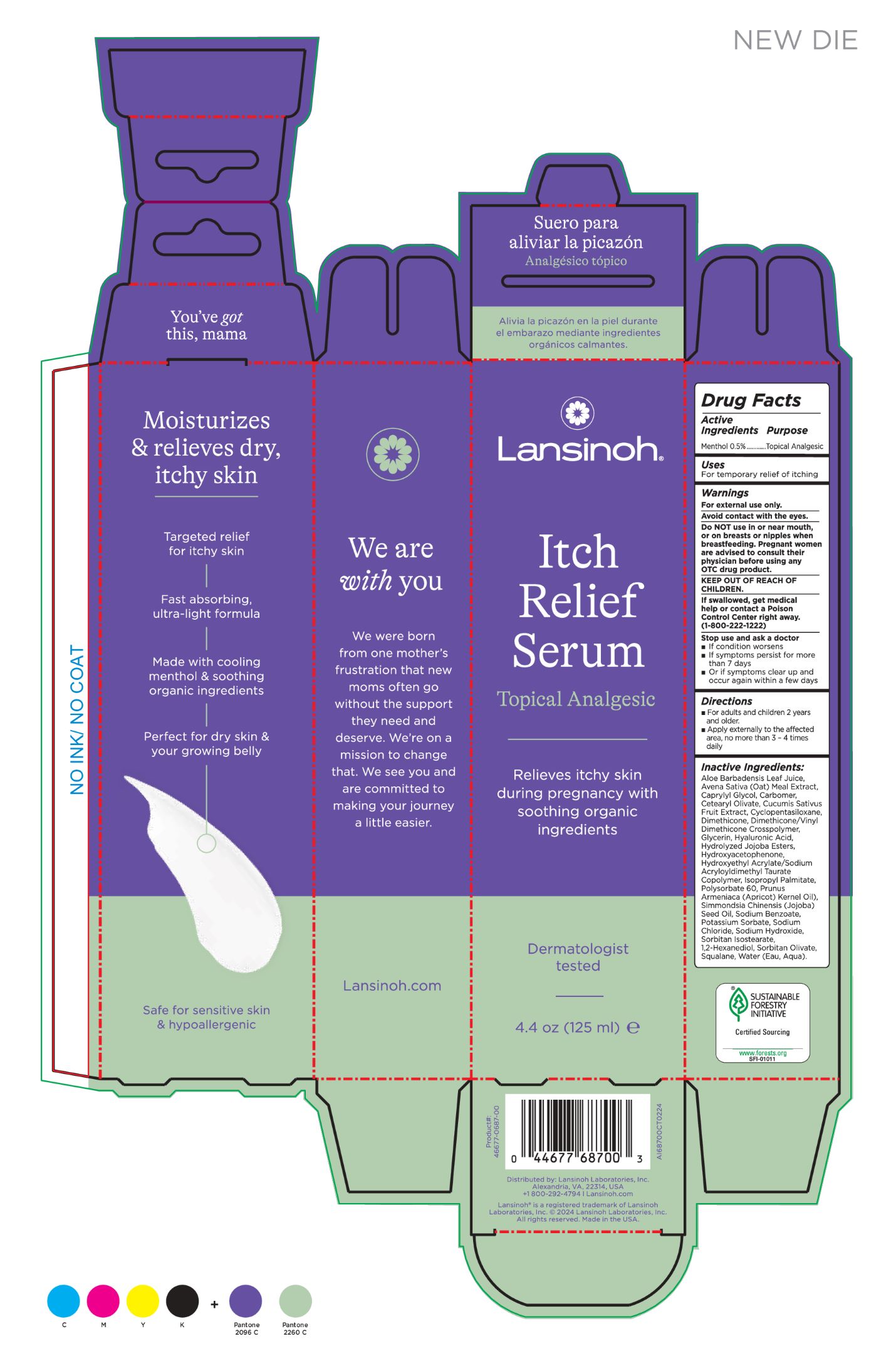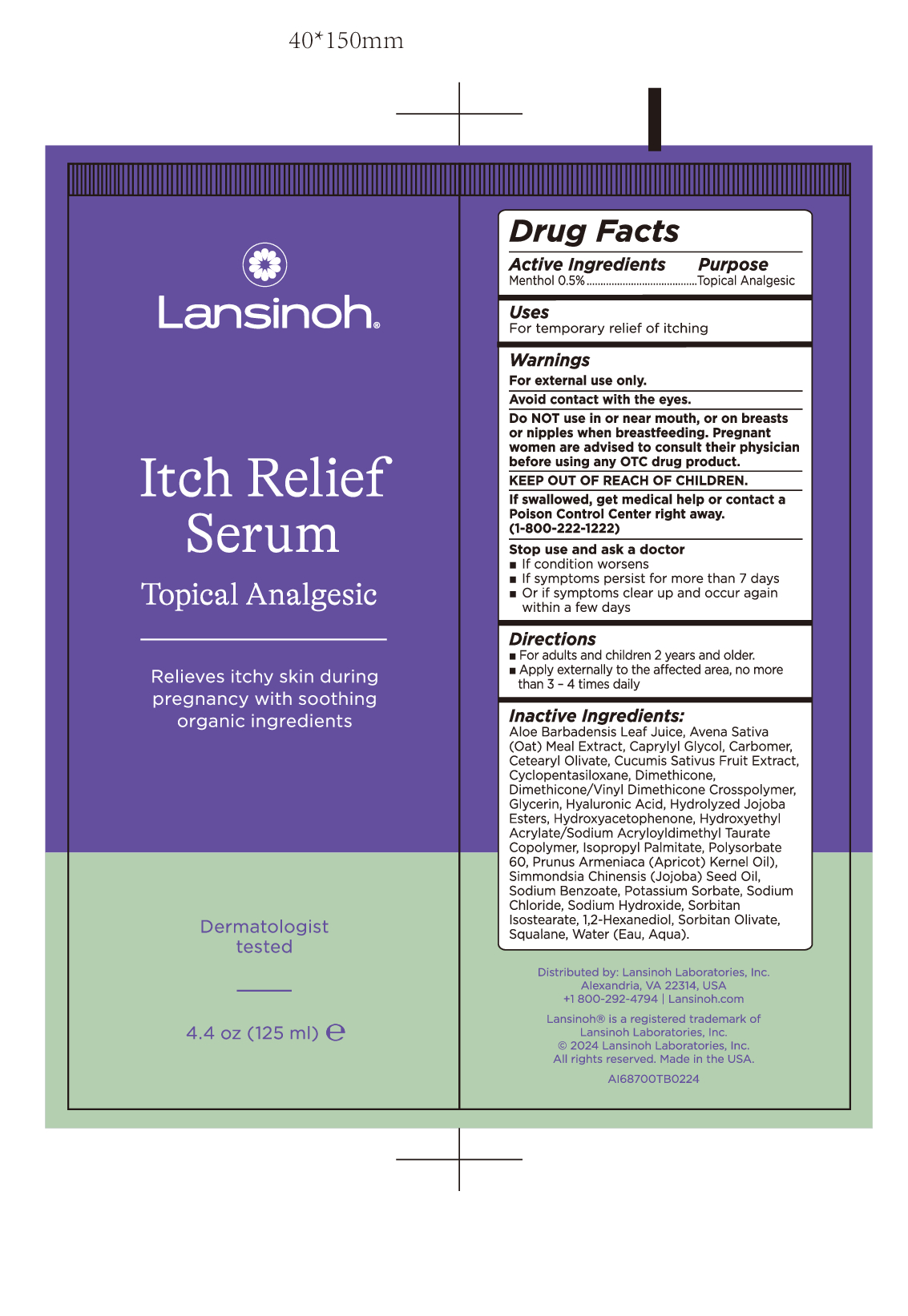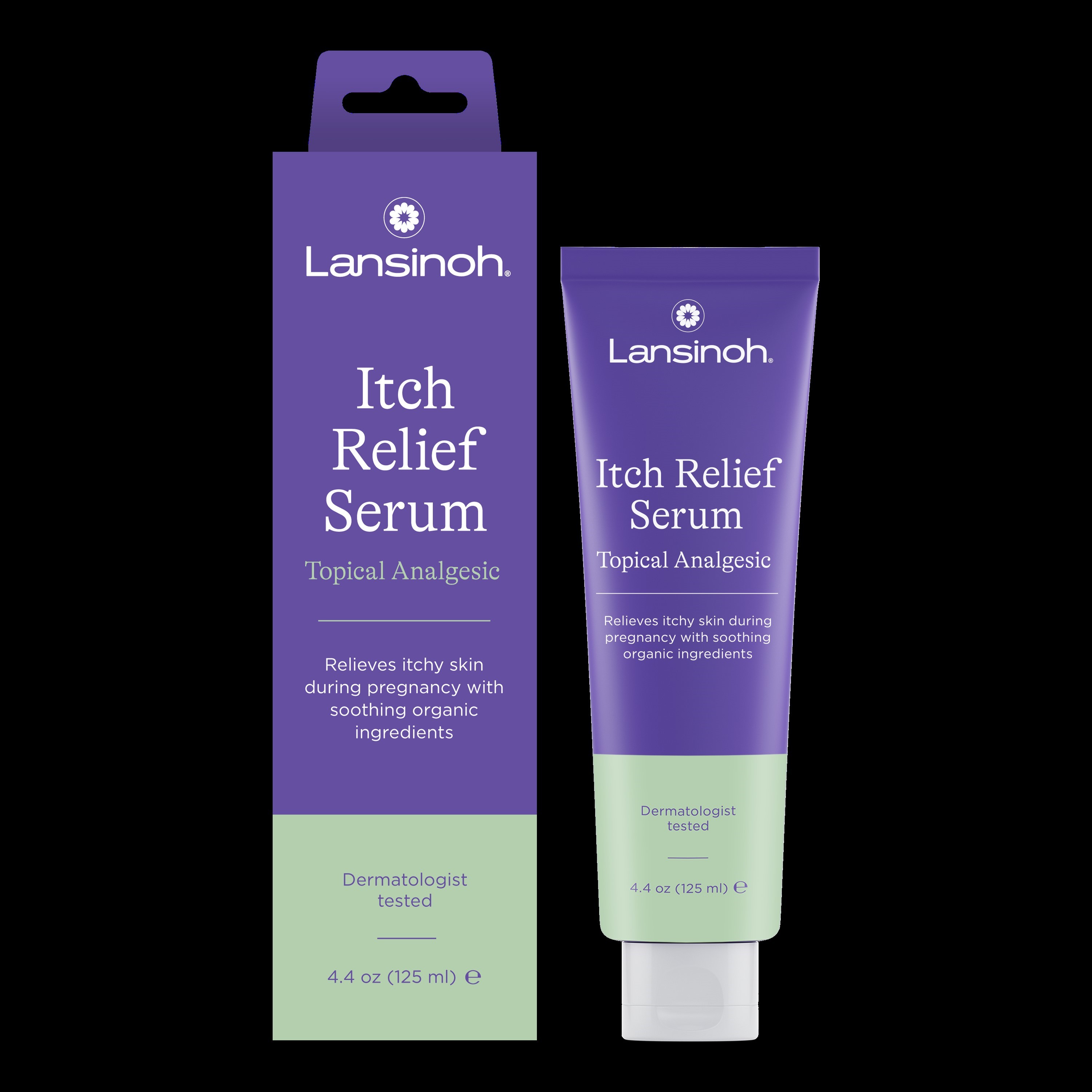 DRUG LABEL: Lansinoh Anti-itch
NDC: 53997-002 | Form: CREAM
Manufacturer: Lansinoh Laboratories Inc
Category: otc | Type: HUMAN OTC DRUG LABEL
Date: 20241222

ACTIVE INGREDIENTS: MENTHOL 0.5 g/100 mL
INACTIVE INGREDIENTS: CUCUMBER; POTASSIUM SORBATE; SODIUM HYDROXIDE; DIMETHICONE; CYCLOMETHICONE 5; GLYCERIN; SQUALANE; JOJOBA OIL; ISOPROPYL PALMITATE; POLYSORBATE 60; CARBOMER INTERPOLYMER TYPE A (ALLYL SUCROSE CROSSLINKED); HYALURONIC ACID; HYDROXYETHYL ACRYLATE/SODIUM ACRYLOYLDIMETHYL TAURATE COPOLYMER (45000 MPA.S AT 1%); CETEARYL OLIVATE; WATER; HYDROLYZED JOJOBA ESTERS (POTASSIUM SALTS); CAPRYLYL GLYCOL; SORBITAN ISOSTEARATE; SODIUM CHLORIDE; SORBITAN OLIVATE; APRICOT KERNEL OIL; SODIUM BENZOATE; OATMEAL; HYDROXYACETOPHENONE; DIMETHICONE/VINYL DIMETHICONE CROSSPOLYMER (HARD PARTICLE); ALOE VERA LEAF; 1,2-HEXANEDIOL

Lansinoh Anti Itch

Active Ingredients | Purpose
Menthol 0.5% | Topical Analgesic

Stop Use and ask a doctor

- if condition worsens
- if symptoms persist for more than 7 days
- Or if symptoms clear up and occur again withina few days

Do NOT use in or near mouth, or on breasts or nipples when breast feeding.

Pregnant women are advised to consult their physician before using any OTC drug product.

KEEP OUT OF REACH OF CHILDREN

if swallowed, get medical help or contact a Poison Control Center right awau (1-800-222-1222)

PURPOSE

For temporary relief of itching

Stop use and ask a doctor

- If condition worsens
- If symptoms persists for more than 7 days
- Or if symptoms clear up and occur again within a few days

Warnings

For external use only

Avoid contact withthe eyes

Directions

- For adults and children 2 years and older
- Apply externally to the affected area, no more than 3-4 times daily

Inactive Ingredients:
Aloe Barbadensis Leaf Juice, Avena Sativa (Oat) Meal Extract, Caprylyl Glycol, Carbomer, Cetearyl Olivate, Cucumis Sativus Fruit Extract, Cyclopentasiloxane, Dimethicone, Dimethicone/Vinyl Dimethicone Crosspolymer, Glycerin, Hyaluronic Acid, Hydrolyzed Jojoba Esters, Hydroxyacetophenone, Hydroxyethyl Acrylate/Sodium Acryloyldimethyl Taurate Copolymer, Isopropyl Palmitate, Polysorbate 60, Prunus Armeniaca (Apricot) Kernel Oil), Simmondsia Chinensis (Jojoba) Seed Oil, Sodium Benzoate, Potassium Sorbate, Sodium Chloride, Sodium Hydroxide, Sorbitan Isostearate, 1,2-Hexanediol, Sorbitan Olivate, Squalane, Water (Eau, Aqua).

Uses
For temporary relief of itching